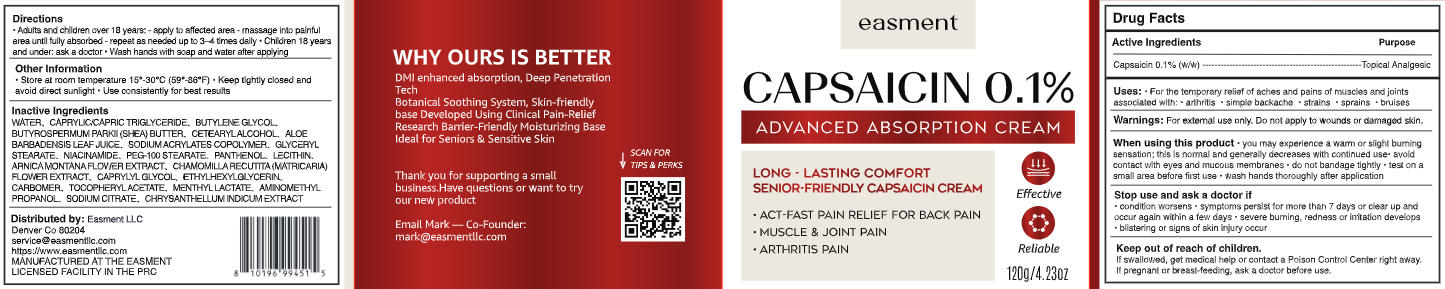 DRUG LABEL: Easment advanced absorption cream
NDC: 87352-001 | Form: CREAM
Manufacturer: Easment LLC
Category: otc | Type: HUMAN OTC DRUG LABEL
Date: 20260120

ACTIVE INGREDIENTS: CAPSAICIN 0.12 g/120 g
INACTIVE INGREDIENTS: PANTHENOL; AMINOMETHYL PROPANOL; MATRICARIA CHAMOMILLA FLOWERING TOP; ARNICA MONTANA FLOWER WATER; CAPRYLYL GLYCOL; BUTYLENE GLYCOL; MENTHYL LACTATE; CAPRYLIC/CAPRIC TRIGLYCERIDE; BUTYROSPERMUM PARKII (SHEA) BUTTER; SODIUM ACRYLATES CROSSPOLYMER-2; GLYCERYL STEARATE; SODIUM CITRATE; ALOE BARBADENSIS LEAF JUICE; ALPHA-TOCOPHEROL ACETATE; WATER; CETEARYL ALCOHOL; ETHYLHEXYLGLYCERIN; CARBOMER; NIACINAMIDE; PEG-100 STEARATE; CHRYSANTHELLUM INDICUM FLOWER OIL; LECITHIN, SOYBEAN

Absorption cream-Initial-66

ACTIVE INGREDIENT

Capsaicin 0.1%

PURPOSE

Topical Analgesic

DOSAGE AND ADMINISTRATION

For the temporary relief of aches and pains of muscles and joints associated with: arthritis, simple backache, strains, sprains, bruises

WARNINGS

For external use only. Do not apply to wounds or damaged skin.

WHEN USING

You may experience a warm or slight burning sensation; this is normal and generally decreases with continued use. avoid contact with eyes and mucous membranes.do not bandage tightly.test on asmall area before first use .wash hands thoroughly after application

ASK DOCTOR

- condition worsens
- symptoms persist for more than 7 days or clear up andoccur again within a few days
- severe burning, redness or irritation develops blistering or signs of skin injury occur

KEEP OUT OF REACH OF CHILDREN

- If swallowed, get medical help or contact a Poison Control Center right away.
- If pregnant or breast-feeding,ask a doctor before use.

INDICATIONS AND USAGE

- Adults and children over 18 years:- apply to affected area - massage into painful area until fully absorbed - repeat as needed up to3-4 times daily
- Children 18 years and under: ask a doctor
- Wash hands with soap and water after applying

OTHER SAFETY INFORMATION

Store at room temperature 15-30C(59-86F).Keep tightly closed and avoid direct sunlight.Use consistently for best results

INACTIVE INGREDIENT

WATER、 CAPRYLIC/CAPRIC TRIGLYCERIDE、 BUTYLENE GLYCOl, BUTYROSPERMUM PARKII (SHEA) BUTTER、 CETEARYLALCOHOL, ALOEBARBADENSIS LEAF JUICE、 SODIUM ACRYLATES COPOLYMER, GLYCERYLSTEARATE、 NIACINAMIDE、 PEG-100 STEARATE、 PANTHENOL、 LECITHIN, ARNICA MONTANA FLOWER EXTRACT、CHAMOMILLA RECUTITA (MATRICARIA)FLOWER EXTRACT、 CAPRYLYL GLYCOL, ETHYLHEXYL GLYCERIN,CARBOMER, TOCOPHERYL ACETATE、 MENTHYL LACTATE、 AMINOMETHYL PROPANOL,SODIUM CITRATE, CHRYSANTHELLUM INDICUM EXTRACT